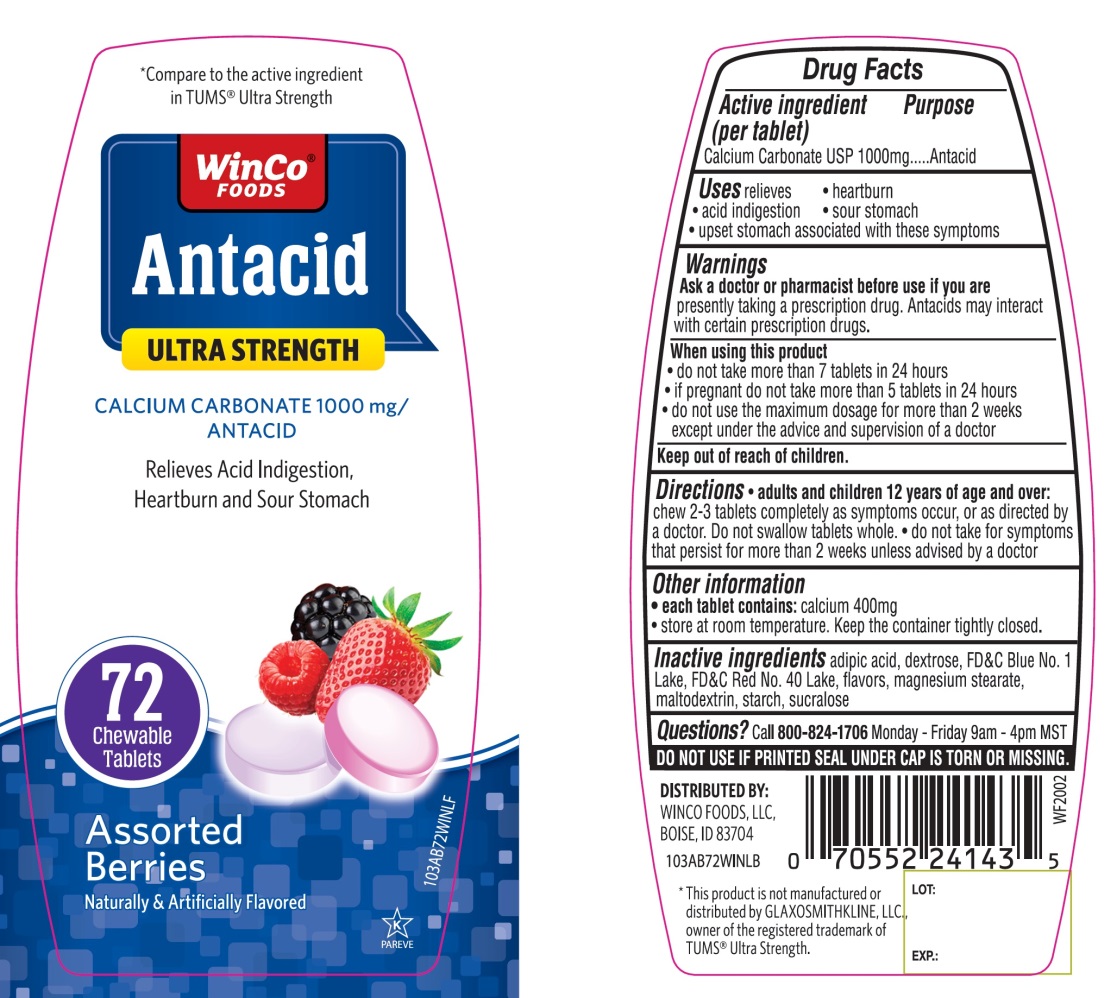 DRUG LABEL: WinCo FOODS Antacid

NDC: 67091-358 | Form: TABLET, CHEWABLE
Manufacturer: WINCO FOODS, LLC
Category: otc | Type: HUMAN OTC DRUG LABEL
Date: 20251202

ACTIVE INGREDIENTS: CALCIUM CARBONATE 1000 mg/1 1
INACTIVE INGREDIENTS: ADIPIC ACID; DEXTROSE, UNSPECIFIED FORM; FD&C BLUE NO. 1; FD&C RED NO. 40; MAGNESIUM STEARATE; MALTODEXTRIN; STARCH, CORN; SUCRALOSE

WinCo FOODS Antacid Ultra Strength Drug Facts

Active ingredient (per tablet)

Calcium Carbonate USP 1000 mg

Purpose

Antacid

Uses

relieves

- heartburn
- sour stomach
- acid indigestion
- upset stomach associated with these symptoms

Warnings

Ask a doctor or pharmacist before use if you are

presently taking a prescription drug. Antacids may interact with certain prescription drugs.

When using this product

- do not take more than 7 tablets in 24 hours
- if pregnant do not take more than 5 tablets in 24 hours
- do not use the maximum dosage for more than 2 weeks except under the advice and supervision of a doctor

Directions

- adults and children 12 years of age and over:chew 2-3 tablets as symptoms occur, or as directed by a doctor
- do not take for symptoms that persist for more than 2 weeks unless advised by a doctor

Other information

- each tablet contains:calcium 400mg
- store at room temperature. Keep the container tightly closed.

Inactive ingredients

adipic acid, dextrose, FD&C Blue No. 1, FD&C Red No. 40, flavors, magnesium stearate, maltodextrin, starch, sucralose

Questions or Comments?

Call 1-800-824-1706 Monday – Friday 9am – 4pm MST

Principal Display Panel

WinCo®FOODS

Compare to the active ingredient TUMS®Ultra Strength

Antacid

ULTRA STRENGTH

NDC 67091-358-72

CALCIUM CARBONATE 1000 mg/ANTACID

Relieves of Acid Indigestion, Heartburn and Sour Stomach

72 Chewable Tablets

Assorted Berries Flavor

Naturally and Artificially Flavored

K PAREVE

DO NOT USE IF PRINTED SEAL UNDER CAP IS TORN OR MISSING.

DISTRIBUTED BY:

WINCO FOODS, LLC,

BOISE, ID 83704

GLUTEN –FREE

*This product is not manufactured or distributed by GLAXOSMITHKLINE, LLC, owner of the registered trademark of TUMS® Ultra Strength.